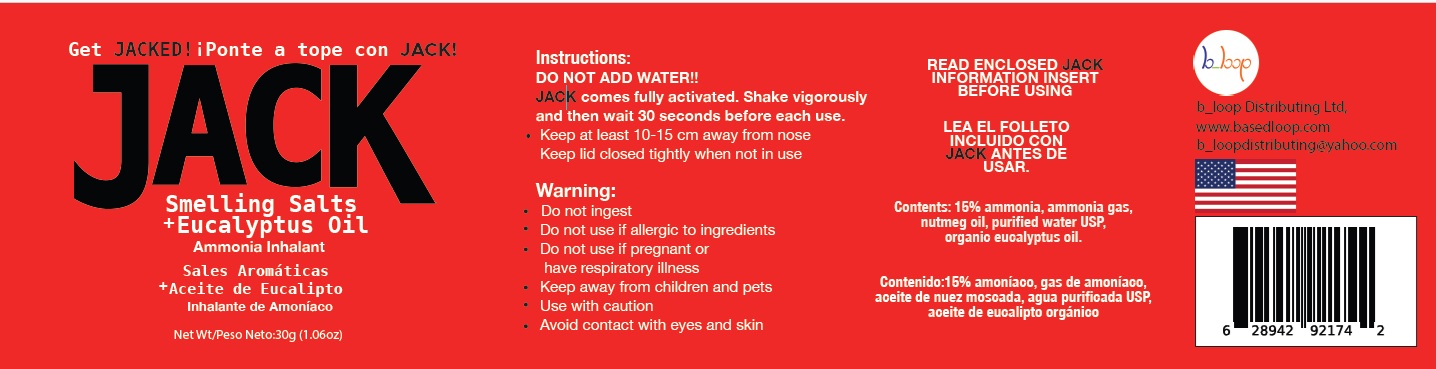 DRUG LABEL: JACK Smelling Salts for Athletes and Eucalyptus Oil
NDC: 85934-001 | Form: INHALANT
Manufacturer: b_loop Distributing Ltd.
Category: otc | Type: HUMAN OTC DRUG LABEL
Date: 20250728

ACTIVE INGREDIENTS: AMMONIUM CARBONATE 15 g/100 g; AMMONIA 15 g/100 g; EUCALYPTUS OIL 10 g/100 g
INACTIVE INGREDIENTS: NUTMEG OIL; WATER

Active Ingredient (s)

ammonium carbonate 15%

eucalyptus oil 10%

ammonia 15%

Purpose

To treat and prevent fainting

Uses

To treat and prevent fainting

Warnings

- Do not ingest.
- Do not use if allergic to ingredients.
- Do not use if pregnant, lactating, or have a respiratory illness or heart disease
- keep away from children and pets
- Avoid contact with eyes and skin.
- Use with caution.

Directions

- With the cap closed tightly, shake the bottle vigorously for 10 seconds or more.
- The wait at least 10 seconds.
- Remove cap, keep bottle at least six inches away from face and inhale cautiously through nose.

Inactive Ingredients

Nutmeg oil, purified water USP